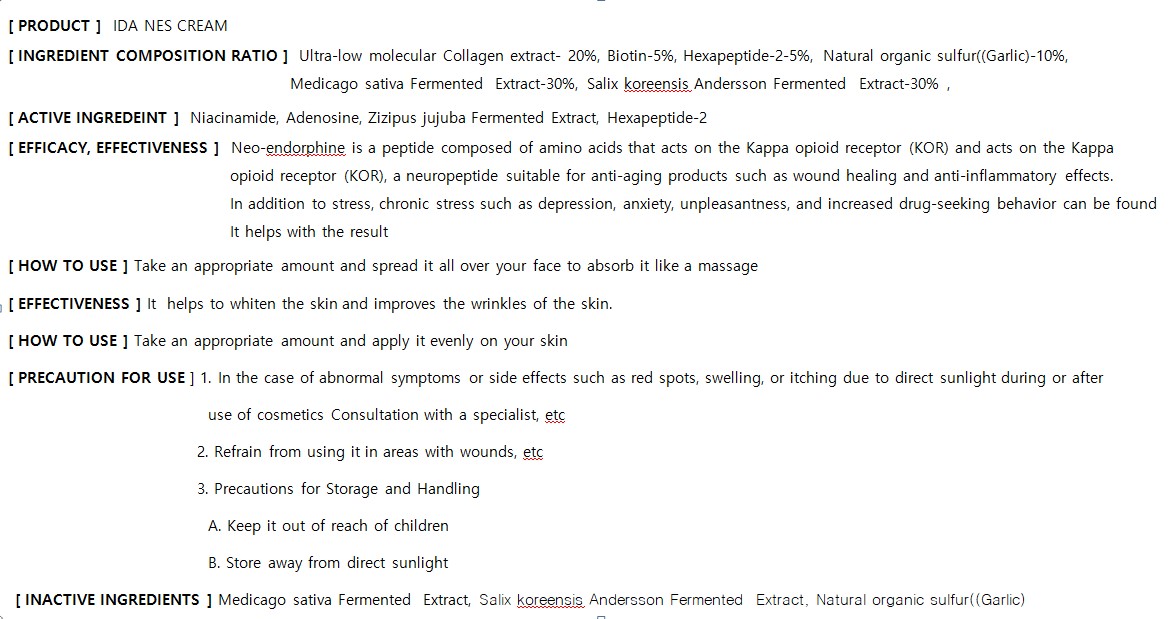 DRUG LABEL: IDA NESCREAM
NDC: 82237-0007 | Form: CREAM
Manufacturer: NFC LIFE SCIENCE CO.,LTD
Category: otc | Type: HUMAN OTC DRUG LABEL
Date: 20240222

ACTIVE INGREDIENTS: NIACINAMIDE 0.04 g/100 mL
INACTIVE INGREDIENTS: WATER

ACTIVE INGREDIENT

Niacinamide, Adenosine, Zizipus jujuba Fermented Extract, Hexapeptide-2

INACTIVE INGREDIENT

Ultra-low molecular Collagen extract- 20%, Biotin-5%, Hexapeptide-2-5%, Natural organic sulfur((Garlic)-10%,

Medicago sativa Fermented Extract-30%, Salix koreensis Andersson Fermented Extract-30%

PURPOSE

Neo-endorphine is a peptide composed of amino acids that acts on the Kappa opioid receptor (KOR) and acts on the Kappa

opioid receptor (KOR), a neuropeptide suitable for anti-aging products such as wound healing and anti-inflammatory effects.

In addition to stress, chronic stress such as depression, anxiety, unpleasantness, and increased drug-seeking behavior can be found

It helps with the result

Keep out of reach of the children

INDICATIONS AND USAGE

] Take an appropriate amount and apply it evenly on your skin

WARNINGS

1.In the case of abnormal symptoms or sid eeffects suchasredspots,swelling,oritchingduetodirectsunlightduringorafter

useofcosmeticsConsultationwithaspecialist,etc

Refrainfromusingitinareaswithwounds, etc

PrecautionsforStorageand Handling

Keepitoutofreachof children
Storeawayfromdirectsunlight

DOSAGE AND ADMINISTRATION

for external use only